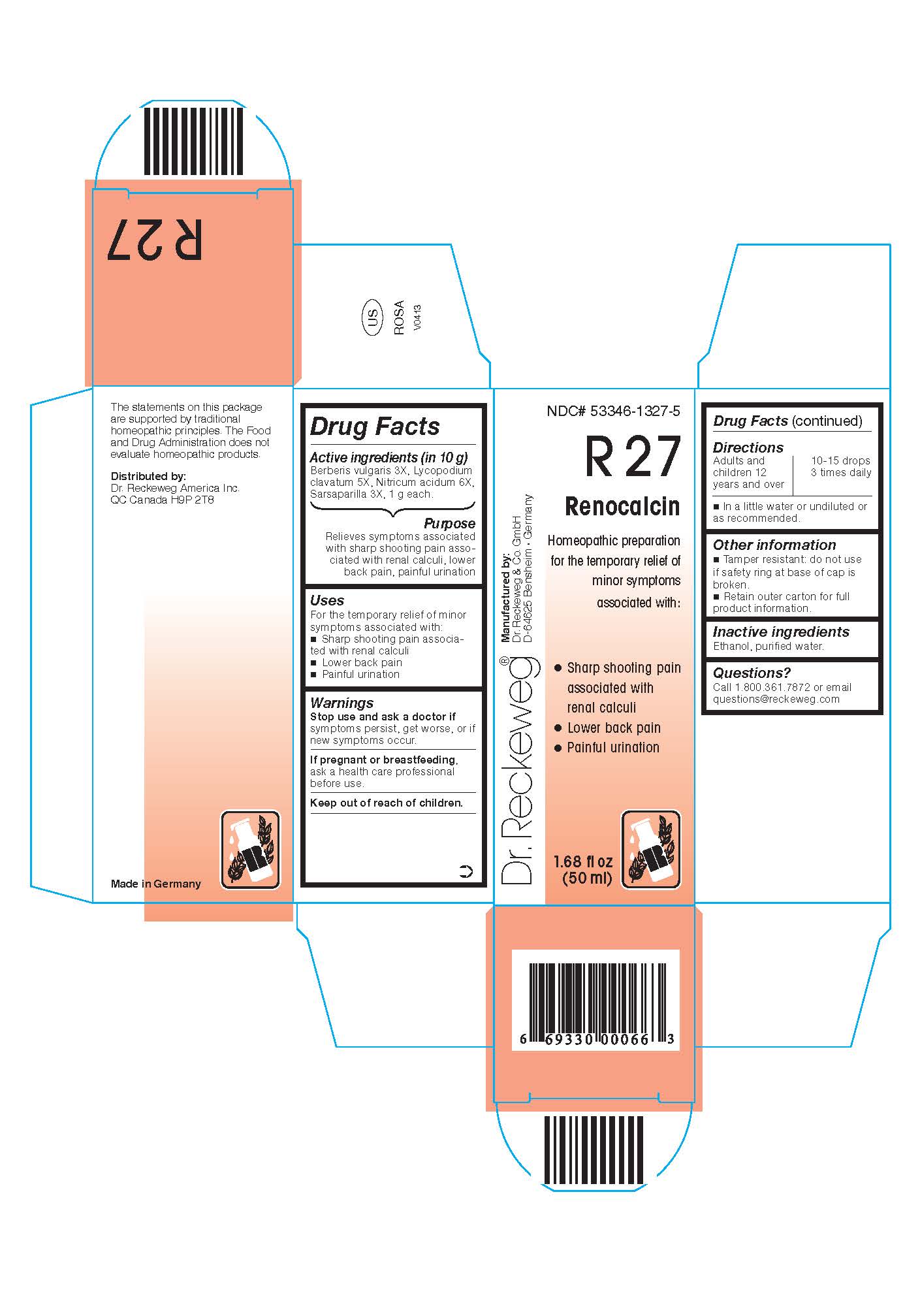 DRUG LABEL: DR. RECKEWEG R27 Renocalcin
NDC: 53346-1327 | Form: LIQUID
Manufacturer: PHARMAZEUTISCHE FABRIK DR. RECKEWEG & CO
Category: homeopathic | Type: HUMAN OTC DRUG LABEL
Date: 20130404

ACTIVE INGREDIENTS: BERBERIS VULGARIS ROOT BARK 3 [hp_X]/50 mL; LYCOPODIUM CLAVATUM SPORE 5 [hp_X]/50 mL; NITRIC ACID 6 [hp_X]/50 mL; SMILAX REGELII ROOT 3 [hp_X]/50 mL
INACTIVE INGREDIENTS: ALCOHOL; WATER

DR. RECKEWEG R27 Renocalcin

Active ingredients:

Berberis vulgaris 3X, Lycopodium clavatum 5X, Nitricum acidum 6X, Sarsaparilla 3X, 1 g each in 10 g.

Purpose

Relieves symptoms associated with sharp shooting pain associated with renal calculi, lower back pains, painful urination

Uses

For the temporary relief of minor symptoms associated with:

- Sharp shooting pain associated with renal calculi
- Lower back pains
- Painful urination

Warnings

Stop use and ask a doctor if symptoms persist, get worse, or if new symptoms occur.

PREGNANCY OR BREAST FEEDING

If pregnant or breastfeeding, ask a health care professional before use.

Keep out of reach of children.

Directions
Adults and children ≥ 12 years 10-15 drops 3 times daily in a little water or undiluted or as recommended.

Other information
Tamper resistant: do not use if safety ring at base of cap is broken.

Retain outer carton for full product instructions.

Inactive ingredients

Ethanol, purified water.

Questions?
Call 1-800-361-7872 or email questions@reckeweg.com

PACKAGE LABEL

NDC# 53346-1327-5

Dr. Reckeweg R27 Renocalcin

Homeopathic preparation for the temporary relief of minor symptoms associated with:

- Sharp shooting pain associated with renal calculi
- Lower back pains
- Painful urination

Manufactured by:

Dr. Reckeweg Co. GmbH

D-64625 Bensheim

Germany

1.68 fl oz
(50 ml)